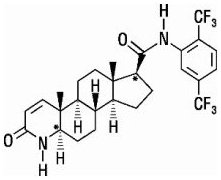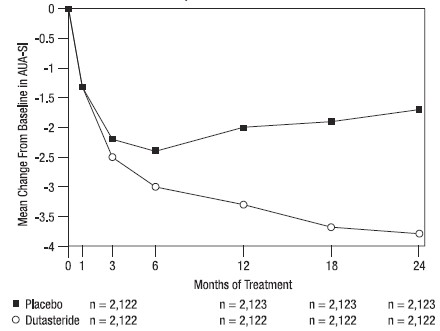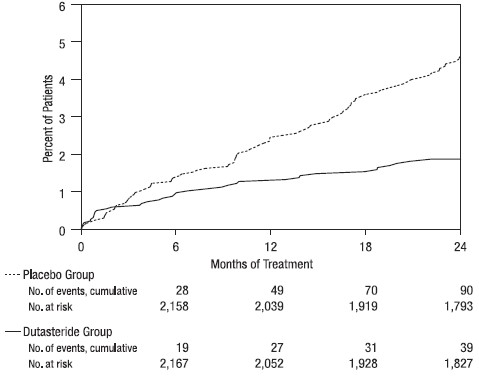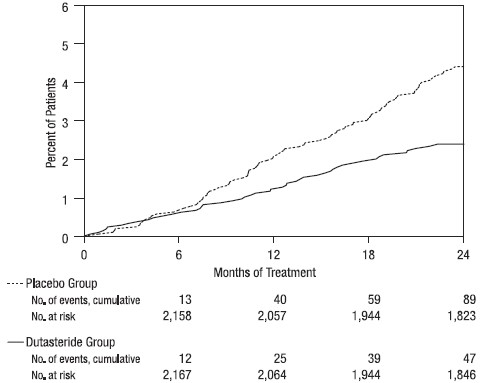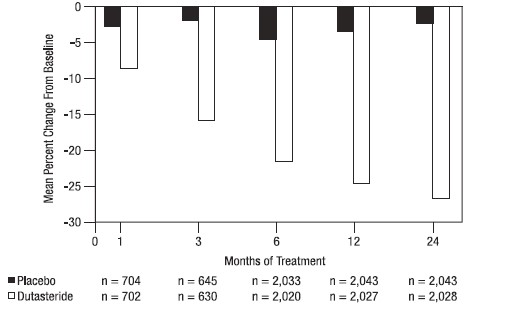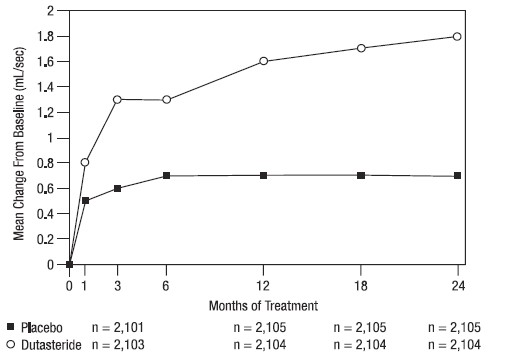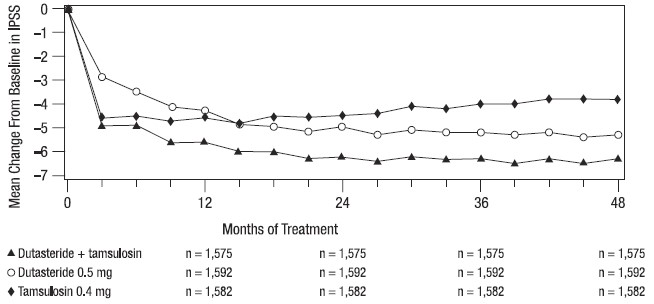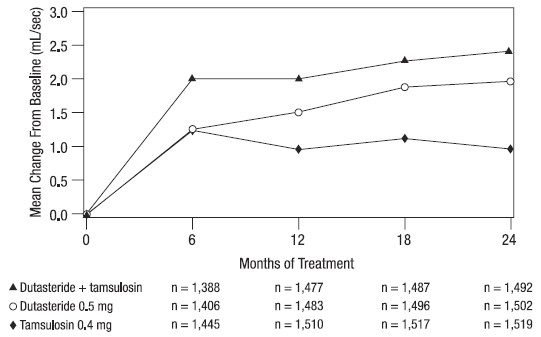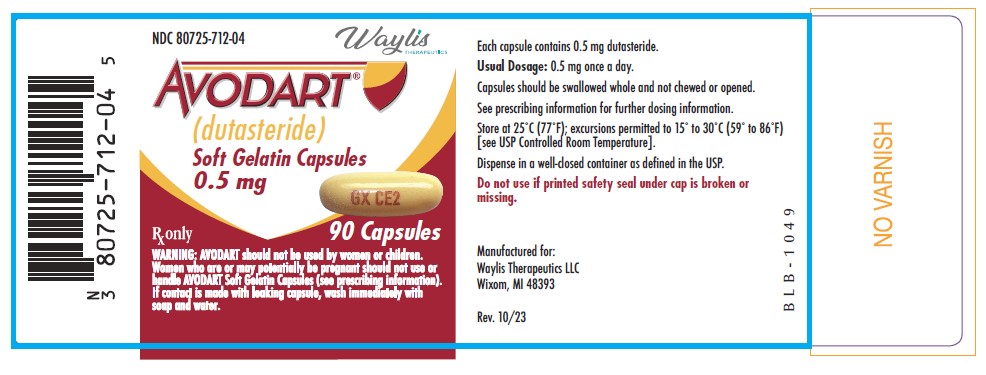 DRUG LABEL: AVODART
NDC: 80725-712 | Form: CAPSULE, LIQUID FILLED
Manufacturer: Waylis Therapeutics LLC
Category: prescription | Type: HUMAN PRESCRIPTION DRUG LABEL
Date: 20250312

ACTIVE INGREDIENTS: DUTASTERIDE 0.5 mg/1 1
INACTIVE INGREDIENTS: BUTYLATED HYDROXYTOLUENE; FERRIC OXIDE YELLOW; GELATIN, UNSPECIFIED; GLYCERIN; GLYCERYL MONO- AND DICAPRYLOCAPRATE

HIGHLIGHTS OF PRESCRIBING INFORMATION

These highlights do not include all the information needed to use AVODART safely and effectively. See full prescribing information for AVODART.
AVODART (dutasteride) soft gelatin capsules
Initial U.S. Approval: 2001

1 INDICATIONS AND USAGE

AVODART is a 5 alpha-reductase inhibitor indicated for the treatment of symptomatic benign prostatic hyperplasia (BPH) in men with an enlarged prostate to: (1.1)

- improve symptoms,
- reduce the risk of acute urinary retention, and
- reduce the risk of the need for BPH-related surgery.

AVODART in combination with the alpha-adrenergic antagonist, tamsulosin, is indicated for the treatment of symptomatic BPH in men with an enlarged prostate. (1.2)

Limitations of Use: AVODART is not approved for the prevention of prostate cancer. (1.3)

2 DOSAGE AND ADMINISTRATION

- Monotherapy: 0.5 mg once daily. (2.1)
- Combination with tamsulosin: 0.5 mg once daily and tamsulosin 0.4 mg once daily. (2.2)
- Dosing considerations: Swallow whole. May take with or without food. (2)

3 DOSAGE FORMS AND STRENGTHS

0.5-mg soft gelatin capsules (3)

4 CONTRAINDICATIONS

- Pregnancy. Dutasteride use is contraindicated in women who are pregnant. (4, 5.4, 8.1)
- Patients with previously demonstrated, clinically significant hypersensitivity (e.g., serious skin reactions, angioedema) to AVODART or other 5 alpha-reductase inhibitors.(4)

5 WARNINGS AND PRECAUTIONS

- AVODART reduces serum prostate-specific antigen (PSA) concentration by approximately 50%. However, any confirmed increase in PSA while on AVODART may signal the presence of prostate cancer and should be evaluated, even if those values are still within the normal range for untreated men. (5.1)
- AVODART may increase the risk of high-grade prostate cancer. (5.2, 6.1)
- Prior to initiating treatment with AVODART, consideration should be given to other urological conditions that may cause similar symptoms. (5.3)
- Women who are pregnant or may be pregnant should not handle AVODART capsules due to potential risk to a male fetus. (5.4, 8.1)
- Patients should not donate blood until 6 months after their last dose of AVODART. (5.5)

6 ADVERSE REACTIONS

The most common adverse reactions, reported in ≥1% of subjects treated with AVODART and more commonly than in subjects treated with placebo, are impotence, decreased libido, ejaculation disorders, and breast disorders. (6.1)

To report SUSPECTED ADVERSE REACTIONS, contact Waylis Therapeutics LLC at 888-514-4727 or FDA at 1-800-FDA-1088 or www.fda.gov/medwatch.

7 DRUG INTERACTIONS

Use with caution in patients taking potent, chronic cytochrome P450 (CYP)3A4 enzyme inhibitors (e.g., ritonavir). (7)

FULL PRESCRIBING INFORMATION

1 INDICATIONS AND USAGE

1.1 Monotherapy

AVODART (dutasteride) soft gelatin capsules are indicated for the treatment of symptomatic benign prostatic hyperplasia (BPH) in men with an enlarged prostate to:

- improve symptoms,
- reduce the risk of acute urinary retention (AUR), and
- reduce the risk of the need for BPH-related surgery.

1.2 Combination with Alpha-adrenergic Antagonist

AVODART in combination with the alpha-adrenergic antagonist, tamsulosin, is indicated for the treatment of symptomatic BPH in men with an enlarged prostate.

1.3 Limitations of Use

AVODART is not approved for the prevention of prostate cancer.

2 DOSAGE AND ADMINISTRATION

The capsules should be swallowed whole and not chewed or opened, as contact with the capsule contents may result in irritation of the oropharyngeal mucosa. AVODART may be administered with or without food.

2.1 Monotherapy

The recommended dose of AVODART is 1 capsule (0.5 mg) taken once daily.

2.2 Combination with Alpha-adrenergic Antagonist

The recommended dose of AVODART is 1 capsule (0.5 mg) taken once daily and tamsulosin 0.4 mg taken once daily.

3 DOSAGE FORMS AND STRENGTHS

0.5-mg, opaque, dull yellow, gelatin capsules imprinted with “GX CE2” in red ink on one side.

4 CONTRAINDICATIONS

AVODART is contraindicated for use in:

- Pregnancy. Dutasteride use is contraindicated in women who are pregnant. In animal reproduction and developmental toxicity studies, dutasteride inhibited development of male fetus external genitalia. Therefore, AVODART may cause fetal harm when administered to a pregnant woman [see Warnings and Precautions (5.4), Use in Specific Populations (8.1)].
- Patients with previously demonstrated clinically significant hypersensitivity (e.g., serious skin reactions, angioedema) to AVODART or other 5 alpha-reductase inhibitors [see Adverse Reactions (6.2)].

5 WARNINGS AND PRECAUTIONS

5.1 Effects on Prostate-Specific Antigen (PSA) and the Use of PSA in Prostate Cancer Detection

In clinical trials, AVODART reduced serum PSA concentration by approximately 50% within 3 to 6 months of treatment. This decrease was predictable over the entire range of PSA values in subjects with symptomatic BPH, although it may vary in individuals. AVODART may also cause decreases in serum PSA in the presence of prostate cancer. To interpret serial PSAs in men taking AVODART, a new PSA baseline should be established at least 3 months after starting treatment and PSA monitored periodically thereafter. Any confirmed increase from the lowest PSA value while on AVODART may signal the presence of prostate cancer and should be evaluated, even if PSA levels are still within the normal range for men not taking a 5 alpha-reductase inhibitor. Noncompliance with AVODART may also affect PSA test results.

To interpret an isolated PSA value in a man treated with AVODART for 3 months or more, the PSA value should be doubled for comparison with normal values in untreated men. The free-to-total PSA ratio (percent free PSA) remains constant, even under the influence of AVODART. If clinicians elect to use percent free PSA as an aid in the detection of prostate cancer in men receiving AVODART, no adjustment to its value appears necessary.

Coadministration of dutasteride and tamsulosin resulted in similar changes to serum PSA as dutasteride monotherapy.

5.2 Increased Risk of High-grade Prostate Cancer

In men aged 50 to 75 years with a prior negative biopsy for prostate cancer and a baseline PSA between 2.5 ng/mL and 10.0 ng/mL taking AVODART in the 4-year Reduction by Dutasteride of Prostate Cancer Events (REDUCE) trial, there was an increased incidence of Gleason score 8-10 prostate cancer compared with men taking placebo (AVODART 1.0% versus placebo 0.5%) [see Indications and Usage (1.3), Adverse Reactions (6.1)]. In a 7-year placebo-controlled clinical trial with another 5 alpha-reductase inhibitor (finasteride 5 mg, PROSCAR), similar results for Gleason score 8-10 prostate cancer were observed (finasteride 1.8% versus placebo 1.1%).

5 alpha-reductase inhibitors may increase the risk of development of high-grade prostate cancer. Whether the effect of 5 alpha-reductase inhibitors to reduce prostate volume or trial-related factors impacted the results of these trials has not been established.

5.3 Evaluation for Other Urological Diseases

Prior to initiating treatment with AVODART, consideration should be given to other urological conditions that may cause similar symptoms. In addition, BPH and prostate cancer may coexist.

5.4 Transdermal Exposure of AVODART in Pregnant Women—Risk to Male Fetus

AVODART capsules should not be handled by women who are pregnant or may be pregnant. Dutasteride can be absorbed through the skin and could result in unintended fetal exposure and potential risk to a male fetus. If a pregnant woman comes in contact with leaking dutasteride capsules, the contact area should be washed immediately with soap and water [see Use in Specific Populations (8.1)]. Dutasteride can be absorbed through the skin based on animal studies [see Nonclinical Toxicology (13.2)].

5.5 Blood Donation

Men being treated with AVODART should not donate blood until at least 6 months have passed following their last dose. The purpose of this deferred period is to prevent administration of dutasteride to a pregnant female transfusion recipient.

5.6 Effect on Semen Characteristics

The effects of dutasteride 0.5 mg/day on semen characteristics were evaluated in healthy men throughout 52 weeks of treatment and 24 weeks of post‑treatment follow‑up. At 52 weeks, compared with placebo, dutasteride treatment resulted in mean reduction in total sperm count, semen volume, and sperm motility; the effects on total sperm count were not reversible after 24 weeks of follow-up. Sperm concentration and sperm morphology were unaffected and mean values for all semen parameters remained within the normal range at all timepoints. The clinical significance of the effect of dutasteride on semen characteristics for an individual patient’s fertility is not known [see Use in Specific Populations (8.3)].

6 ADVERSE REACTIONS

6.1 Clinical Trials Experience

Because clinical trials are conducted under widely varying conditions, adverse reaction rates observed in the clinical trials of a drug cannot be directly compared with rates in the clinical trial of another drug and may not reflect the rates observed in practice.

From clinical trials with AVODART as monotherapy or in combination with tamsulosin:

- The most common adverse reactions reported in subjects receiving AVODART were impotence, decreased libido, breast disorders (including breast enlargement and tenderness), and ejaculation disorders. The most common adverse reactions reported in subjects receiving combination therapy (AVODART plus tamsulosin) were impotence, decreased libido, breast disorders (including breast enlargement and tenderness), ejaculation disorders, and dizziness. Ejaculation disorders occurred significantly more in subjects receiving combination therapy (11%) compared with those receiving AVODART (2%) or tamsulosin (4%) as monotherapy.
- Trial withdrawal due to adverse reactions occurred in 4% of subjects receiving AVODART and 3% of subjects receiving placebo in placebo-controlled trials with AVODART. The most common adverse reaction leading to trial withdrawal was impotence (1%).
- In the clinical trial evaluating the combination therapy, trial withdrawal due to adverse reactions occurred in 6% of subjects receiving combination therapy (AVODART plus tamsulosin) and 4% of subjects receiving AVODART or tamsulosin as monotherapy. The most common adverse reaction in all treatment arms leading to trial withdrawal was erectile dysfunction (1% to 1.5%).

Monotherapy

Over 4,300 male subjects with BPH were randomly assigned to receive placebo or 0.5-mg daily doses of AVODART in 3 identical 2-year, placebo-controlled, double-blind, Phase 3 treatment trials, each followed by a 2-year open-label extension. During the double-blind treatment period, 2,167 male subjects were exposed to AVODART, including 1,772 exposed for 1 year and 1,510 exposed for 2 years. When including the open-label extensions, 1,009 male subjects were exposed to AVODART for 3 years and 812 were exposed for 4 years. The population was aged 47 to 94 years (mean age: 66 years) and greater than 90% were white. Table 1 summarizes clinical adverse reactions reported in at least 1% of subjects receiving AVODART and at a higher incidence than subjects receiving placebo.

Table 1. Adverse Reactions Reported in ≥1% of Subjects over a 24-Month Period and More Frequently in the Group Receiving AVODART than the Placebo Group (Randomized, Double-blind, Placebo-Controlled Trials Pooled) by Time of Onset
Adverse Reaction | Adverse Reaction Time of Onset
Adverse Reaction | Months 0‑6 | Months 7‑12 | Months 13‑18 | Months 19‑24
AVODART (n) | (n = 2,167) | (n = 1,901) | (n = 1,725) | (n = 1,605)
Placebo (n) | (n = 2,158) | (n = 1,922) | (n = 1,714) | (n = 1,555)
Impotencea
AVODART | 4.7% | 1.4% | 1.0% | 0.8%
Placebo | 1.7% | 1.5% | 0.5% | 0.9%
Decreased libidoa
AVODART | 3.0% | 0.7% | 0.3% | 0.3%
Placebo | 1.4% | 0.6% | 0.2% | 0.1%
Ejaculation disordersa
AVODART | 1.4% | 0.5% | 0.5% | 0.1%
Placebo | 0.5% | 0.3% | 0.1% | 0.0%
Breast disordersb
AVODART | 0.5% | 0.8% | 1.1% | 0.6%
Placebo | 0.2% | 0.3% | 0.3% | 0.1%
a These sexual adverse reactions are associated with dutasteride treatment (including monotherapy and combination with tamsulosin). These adverse reactions may persist after treatment discontinuation. The role of dutasteride in this persistence is unknown.
b Includes breast tenderness and breast enlargement.

Long-term Treatment (Up to 4 Years)

High-grade Prostate Cancer: The REDUCE trial was a randomized, double-blind, placebo-controlled trial that enrolled 8,231 men aged 50 to 75 years with a serum PSA of 2.5 ng/mL to 10 ng/mL and a negative prostate biopsy within the previous 6 months. Subjects were randomized to receive placebo (n = 4,126) or 0.5-mg daily doses of AVODART (n = 4,105) for up to 4 years. The mean age was 63 years and 91% were white. Subjects underwent protocol-mandated scheduled prostate biopsies at 2 and 4 years of treatment or had “for-cause biopsies” at non-scheduled times if clinically indicated. There was a higher incidence of Gleason score 8-10 prostate cancer in men receiving AVODART (1.0%) compared with men on placebo (0.5%) [see Indications and Usage (1.3), Warnings and Precautions (5.2)]. In a 7-year placebo-controlled clinical trial with another 5 alpha-reductase inhibitor (finasteride 5 mg, PROSCAR), similar results for Gleason score 8-10 prostate cancer were observed (finasteride 1.8% versus placebo 1.1%).

No clinical benefit has been demonstrated in patients with prostate cancer treated with AVODART.

Reproductive and Breast Disorders

In the 3 pivotal placebo-controlled BPH trials with AVODART, each 4 years in duration, there was no evidence of increased sexual adverse reactions (impotence, decreased libido, and ejaculation disorder) or breast disorders with increased duration of treatment. Among these 3 trials, there was 1 case of breast cancer in the dutasteride group and 1 case in the placebo group. No cases of breast cancer were reported in any treatment group in the 4-year CombAT trial or the 4-year REDUCE trial.

The relationship between long-term use of dutasteride and male breast neoplasia is currently unknown.

Combination with Alpha-blocker Therapy (CombAT)

Over 4,800 male subjects with BPH were randomly assigned to receive 0.5-mg AVODART, 0.4-mg tamsulosin, or combination therapy (0.5-mg AVODART plus 0.4-mg tamsulosin) administered once daily in a 4-year double-blind trial. Overall, 1,623 subjects received monotherapy with AVODART; 1,611 subjects received monotherapy with tamsulosin; and 1,610 subjects received combination therapy. The population was aged 49 to 88 years (mean age: 66 years) and 88% were white. Table 2 summarizes adverse reactions reported in at least 1% of subjects in the combination group and at a higher incidence than subjects receiving monotherapy with AVODART or tamsulosin.

Table 2. Adverse Reactions Reported over a 48-Month Period in ≥1% of Subjects and More Frequently in the Coadministration Therapy Group than the Groups Receiving Monotherapy with AVODART or Tamsulosin (CombAT) by Time of Onset
Adverse Reaction | Adverse Reaction Time of Onset
Adverse Reaction | Year 1
Adverse Reaction | Months 0‑6 | Months 7‑12 | Year 2 | Year 3 | Year 4
Combinationa | (n = 1,610) | (n = 1,527) | (n = 1,428) | (n = 1,283) | (n = 1,200)
AVODART | (n = 1,623) | (n = 1,548) | (n = 1,464) | (n = 1,325) | (n = 1,200)
Tamsulosin | (n = 1,611) | (n = 1,545) | (n = 1,468) | (n = 1,281) | (n = 1,112)
Ejaculation disordersb,c
Combination | 7.8% | 1.6% | 1.0% | 0.5% | <0.1%
AVODART | 1.0% | 0.5% | 0.5% | 0.2% | 0.3%
Tamsulosin | 2.2% | 0.5% | 0.5% | 0.2% | 0.3%
Impotencec,d
Combination | 5.4% | 1.1% | 1.8% | 0.9% | 0.4%
AVODART | 4.0% | 1.1% | 1.6% | 0.6% | 0.3%
Tamsulosin | 2.6% | 0.8% | 1.0% | 0.6% | 1.1%
Decreased libidoc,e
Combination | 4.5% | 0.9% | 0.8% | 0.2% | 0.0%
AVODART | 3.1% | 0.7% | 1.0% | 0.2% | 0.0%
Tamsulosin | 2.0% | 0.6% | 0.7% | 0.2% | <0.1%
Breast disordersf
Combination | 1.1% | 1.1% | 0.8% | 0.9% | 0.6%
AVODART | 0.9% | 0.9% | 1.2% | 0.5% | 0.7%
Tamsulosin | 0.4% | 0.4% | 0.4% | 0.2% | 0.0%
Dizziness
Combination | 1.1% | 0.4% | 0.1% | <0.1% | 0.2%
AVODART | 0.5% | 0.3% | 0.1% | <0.1% | <0.1%
Tamsulosin | 0.9% | 0.5% | 0.4% | <0.1% | 0.0%
a Combination = AVODART 0.5 mg once daily plus tamsulosin 0.4 mg once daily.
b Includes anorgasmia, retrograde ejaculation, semen volume decreased, orgasmic sensation decreased, orgasm abnormal, ejaculation delayed, ejaculation disorder, ejaculation failure, and premature ejaculation.
c These sexual adverse reactions are associated with dutasteride treatment (including monotherapy and combination with tamsulosin). These adverse reactions may persist after treatment discontinuation. The role of dutasteride in this persistence is unknown.
d Includes erectile dysfunction and disturbance in sexual arousal.
e Includes libido decreased, libido disorder, loss of libido, sexual dysfunction, and male sexual dysfunction.
f Includes breast enlargement, gynecomastia, breast swelling, breast pain, breast tenderness, nipple pain, and nipple swelling.

Cardiac Failure: In CombAT, after 4 years of treatment, the incidence of the composite term cardiac failure in the combination therapy group (12/1,610; 0.7%) was higher than in either monotherapy group: AVODART, 2/1,623 (0.1%) and tamsulosin, 9/1,611 (0.6%). Composite cardiac failure was also examined in a separate 4-year placebo-controlled trial evaluating AVODART in men at risk for development of prostate cancer. The incidence of cardiac failure in subjects taking AVODART was 0.6% (26/4,105) compared with 0.4% (15/4,126) in subjects on placebo. A majority of subjects with cardiac failure in both trials had comorbidities associated with an increased risk of cardiac failure. Therefore, the clinical significance of the numerical imbalances in cardiac failure is unknown. No causal relationship between AVODART alone or in combination with tamsulosin and cardiac failure has been established. No imbalance was observed in the incidence of overall cardiovascular adverse events in either trial.

6.2 Postmarketing Experience

The following adverse reactions have been identified during post-approval use of AVODART. Because these reactions are reported voluntarily from a population of uncertain size, it is not always possible to reliably estimate their frequency or establish a causal relationship to drug exposure. These reactions have been chosen for inclusion due to a combination of their seriousness, frequency of reporting, or potential causal connection to AVODART.

Immune System Disorders

Hypersensitivity reactions, including rash, pruritus, urticaria, localized edema, serious skin reactions, and angioedema.

Neoplasms

Male breast cancer.

Psychiatric Disorders

Depressed mood.

Reproductive System and Breast Disorders

Testicular pain and testicular swelling.

7 DRUG INTERACTIONS

7.1 Cytochrome P450 3A Inhibitors

Dutasteride is extensively metabolized in humans by the cytochrome P450 (CYP)3A4 and CYP3A5 isoenzymes. The effect of potent CYP3A4 inhibitors on dutasteride has not been studied. Because of the potential for drug‑drug interactions, use caution when prescribing AVODART to patients taking potent, chronic CYP3A4 enzyme inhibitors (e.g., ritonavir) [see Clinical Pharmacology (12.3)].

7.2 Alpha-adrenergic Antagonists

The administration of AVODART in combination with tamsulosin or terazosin has no effect on the steady-state pharmacokinetics of either alpha-adrenergic antagonist. The effect of administration of tamsulosin or terazosin on dutasteride pharmacokinetic parameters has not been evaluated.

7.3 Calcium Channel Antagonists

Coadministration of verapamil or diltiazem decreases dutasteride clearance and leads to increased exposure to dutasteride. The change in dutasteride exposure is not considered to be clinically significant. No dose adjustment is recommended [see Clinical Pharmacology (12.3)].

7.4 Cholestyramine

Administration of a single 5-mg dose of AVODART followed 1 hour later by 12 g of cholestyramine does not affect the relative bioavailability of dutasteride [see Clinical Pharmacology (12.3)].

7.5 Digoxin

AVODART does not alter the steady-state pharmacokinetics of digoxin when administered concomitantly at a dose of 0.5 mg/day for 3 weeks [see Clinical Pharmacology (12.3)].

7.6 Warfarin

Concomitant administration of AVODART 0.5 mg/day for 3 weeks with warfarin does not alter the steady-state pharmacokinetics of the S- or R-warfarin isomers or alter the effect of warfarin on prothrombin time [see Clinical Pharmacology (12.3)].

8 USE IN SPECIFIC POPULATIONS

8.1 Pregnancy

Risk Summary

AVODART is contraindicated for use in pregnancy because it may cause harm to the male fetus [see Contraindications (4)]. AVODART is not indicated for use in women.

AVODART is a 5 alpha‑reductase inhibitor that prevents conversion of testosterone to dihydrotestosterone (DHT), a hormone necessary for normal development of male genitalia. Abnormalities in the genitalia of male fetuses is an expected physiological consequence of inhibition of this conversion. These results are similar to observations in male infants with genetic 5 alpha‑reductase deficiency.

In the U.S. general population, the estimated background risk of major birth defects and miscarriage in clinically recognized pregnancies is 2% to 4% and 15% to 20%, respectively.

In animal reproduction studies, dutasteride inhibited normal development of external genitalia in male offspring when given to rats or rabbits during organogenesis at less than the maximum recommended human dose (MRHD) of 0.5 mg daily, in the absence of maternal toxicity. At 15 times the MRHD, prolonged pregnancy, decreased reproductive organ weights, and delayed puberty in male offspring were observed in rats, with no-effect levels less than the MRHD of 0.5 mg daily. Increased placental weights in rabbits were also observed, with no-effect levels less than the MRHD of 0.5 mg daily (see Data).

Although dutasteride is secreted into human semen, the drug concentration in the human female partner is approximately 100 times less than concentrations producing abnormalities of male genitalia in animal studies (see Data). In monkeys dosed during organogenesis at blood concentrations comparable to or above levels to which a human female partner is estimated to be exposed, male offspring external genitalia was not adversely affected. No feminization occurred in male offspring of untreated female rats mated to treated male rats even though detectable blood levels of dutasteride were observed in the female rats [see Nonclinical Toxicology (13.1)].

Data

Human Data: The highest measured semen concentration of dutasteride in treated men was 14 ng/mL. Although dutasteride is detected in semen, assuming exposure of a 50‑kg woman to 5 mL of semen and 100% absorption, the woman’s expected dutasteride blood concentration through semen would be about 0.0175 ng/mL. This concentration is approximately 100 times less than blood concentrations producing abnormalities of male genitalia in animal studies. Dutasteride is highly protein bound in human semen (greater than 96%), which may reduce the amount of dutasteride available for vaginal absorption.

Animal Data: In an embryo‑fetal development study in rats, oral administration of dutasteride at 10 times less than the MRHD of 0.5 mg daily (based on average blood levels in men) resulted in feminization of male genitalia in the fetus (decreased anogenital distance at 0.05 mg/kg/day, with a lack of a no-effect level) in the absence of maternal toxicity. In addition, nipple development, hypospadias, and distended preputial glands occurred in fetuses of dams treated at doses of 2.5 mg/kg/day or greater (approximately 15 times the MRHD). Reduced fetal body weight and associated delayed ossification in the presence of maternal toxicity (decreased body weight gain) were observed at maternal exposure approximately 15 times the MRHD (dose of 2.5 mg/kg/day or greater). An increase in stillborn pups was observed in dams treated at 30 mg/kg/day (approximately 111 times the MRHD), with a no-effect level of 12.5 mg/kg/day.

In a rabbit embryo-fetal development study, doses 28 times the MRHD (doses of 30 mg/kg/day or greater), based on average blood levels in men, were administered orally on Gestation Days 7 to 29 (during organogenesis and the late period of external genitalia development). Histological evaluation of the genital papilla of fetuses revealed evidence of feminization of the male fetus as well as fused skull bones and increased placental weights at all doses in the absence of maternal toxicity. A second embryo-fetal development study in rabbits dosed throughout pregnancy (organogenesis and later period of external genitalia development [Gestation Days 6 to 29]) at 0.3 times the MRHD (doses of 0.05 mg/kg/day or greater, with no no-effect level), also produced evidence of feminization of the genitalia in male fetuses and increased placental weights at all doses in the absence of maternal toxicity.

In an embryo-fetal development study, pregnant rhesus monkeys were exposed intravenously during organogenesis (Gestation Days 20 to 100) to a dutasteride blood level comparable to or above the estimated dutasteride exposure of a human female partner. Dutasteride was administered on Gestation Days 20 to 100 (during organogenesis) at doses of 400, 780, 1,325, or 2,010 ng/day (12 monkeys/group). No feminization of male external genitalia of monkey offspring was observed. Reduction of fetal adrenal weights, reduction in fetal prostate weights, and increases in fetal ovarian and testis weights were observed at the highest dose tested. Based on the highest measured semen concentration of dutasteride in treated men (14 ng/mL), these doses in the monkey represent up to 16 times the potential maximum exposure of a 50‑kg human female to 5 mL of semen daily from a dutasteride-treated male, assuming 100% absorption. The dose levels (on a ng/kg basis) administered to monkeys in this study are 32 to 186 times the nominal (ng/kg) dose to which a female would potentially be exposed via the semen. It is not known whether rabbits or rhesus monkeys produce any of the major human metabolites.

In an oral pre- and post-natal development study in rats, feminization of the male genitalia was observed. Decreased anogenital distance was observed at 0.05 times the MRHD and greater (0.05 mg/kg/day and greater), with a lack of a no-effect level, based on average blood levels in men as an estimation of AUC. Hypospadias and nipple development were observed at 2.5 mg/kg/day or greater (14 times the MRHD or greater, with a no-effect level at 0.05 mg/kg/day). Doses of 2.5 mg/kg/day and greater also resulted in prolonged gestation in the parental females, an increase in time to balano-preputial separation in male offspring, a decrease in time to vaginal patency for female offspring, and a decrease in prostate and seminal vesicle weights in male offspring. Increased stillbirths and decreased neonatal viability in offspring were noted at 30 mg/kg/day (102 times the MRHD in the presence of maternal toxicity [decreased body weights]).

8.2 Lactation

Risk Summary

AVODART is not indicated for use in women. There is no information available on the presence of dutasteride in human milk, the effects on the breastfed child, or the effects on milk production.

8.3 Females and Males of Reproductive Potential

Infertility

Males: The effects of dutasteride 0.5 mg/day on semen characteristics were evaluated in normal volunteers aged 18 to 52 years (n = 27 dutasteride, n = 23 placebo) throughout 52 weeks of treatment and 24 weeks of post-treatment follow-up. At 52 weeks, the mean percent reductions from baseline in total sperm count, semen volume, and sperm motility were 23%, 26%, and 18%, respectively, in the dutasteride group when adjusted for changes from baseline in the placebo group. Sperm concentration and sperm morphology were unaffected. After 24 weeks of follow-up, the mean percent change in total sperm count in the dutasteride group remained 23% lower than baseline. While mean values for all semen parameters at all timepoints remained within the normal ranges and did not meet predefined criteria for a clinically significant change (30%), 2 subjects in the dutasteride group had decreases in sperm count of greater than 90% from baseline at 52 weeks, with partial recovery at the 24-week follow-up. The clinical significance of dutasteride’s effect on semen characteristics for an individual patient’s fertility is not known [see Warnings and Precautions (5.6)].

8.4 Pediatric Use

AVODART is not indicated for use in pediatric patients. Safety and effectiveness in pediatric patients have not been established.

8.5 Geriatric Use

Of 2,167 male subjects treated with AVODART in 3 clinical trials, 60% were aged 65 years and older and 15% were aged 75 years and older. No overall differences in safety or efficacy were observed between these subjects and younger subjects. Other reported clinical experience has not identified differences in responses between the elderly and younger patients, but greater sensitivity of some older individuals cannot be ruled out [see Clinical Pharmacology (12.3)].

8.6 Renal Impairment

No dose adjustment is necessary for AVODART in patients with renal impairment [see Clinical Pharmacology (12.3)].

8.7 Hepatic Impairment

The effect of hepatic impairment on dutasteride pharmacokinetics has not been studied. Because dutasteride is extensively metabolized, exposure could be higher in hepatically impaired patients. However, in a clinical trial where 60 subjects received 5 mg (10 times the therapeutic dose) daily for 24 weeks, no additional adverse events were observed compared with those observed at the therapeutic dose of 0.5 mg [see Clinical Pharmacology (12.3)].

10 OVERDOSAGE

In volunteer trials, single doses of dutasteride up to 40 mg (80 times the therapeutic dose) for 7 days have been administered without significant safety concerns. In a clinical trial, daily doses of 5 mg (10 times the therapeutic dose) were administered to 60 subjects for 6 months with no additional adverse effects to those seen at therapeutic doses of 0.5 mg.

There is no specific antidote for dutasteride. Therefore, in cases of suspected overdosage, symptomatic and supportive treatment should be given as appropriate, taking the long half-life of dutasteride into consideration.

11 DESCRIPTION

AVODART is a synthetic 4-azasteroid compound that is a selective inhibitor of both the type 1 and type 2 isoforms of steroid 5 alpha-reductase, an intracellular enzyme that converts testosterone to DHT.

Dutasteride is chemically designated as (5α,17β)-N-{2,5 bis(trifluoromethyl)phenyl}-3-oxo-4-azaandrost-1-ene-17-carboxamide. The empirical formula of dutasteride is C27H30F6N2O2, representing a molecular weight of 528.5 with the following structural formula:

Dutasteride is a white to pale yellow powder with a melting point of 242° to 250°C. It is soluble in ethanol (44 mg/mL), methanol (64 mg/mL), and polyethylene glycol 400 (3 mg/mL), but it is insoluble in water.

Each AVODART soft gelatin capsule, administered orally, contains 0.5 mg of dutasteride dissolved in a mixture of mono-di-glycerides of caprylic/capric acid and butylated hydroxytoluene. The inactive excipients in the capsule shell are ferric oxide (yellow), gelatin (from certified BSE-free bovine sources), glycerin, and titanium dioxide. The soft gelatin capsules are printed with edible red ink.

12 CLINICAL PHARMACOLOGY

12.1 Mechanism of Action

Dutasteride inhibits the conversion of testosterone to DHT. DHT is the androgen primarily responsible for the initial development and subsequent enlargement of the prostate gland. Testosterone is converted to DHT by the enzyme 5 alpha-reductase, which exists as 2 isoforms, type 1 and type 2. The type 2 isoenzyme is primarily active in the reproductive tissues, while the type 1 isoenzyme is also responsible for testosterone conversion in the skin and liver.

Dutasteride is a competitive and specific inhibitor of both type 1 and type 2 5 alpha-reductase isoenzymes, with which it forms a stable enzyme complex. Dissociation from this complex has been evaluated under in vitro and in vivo conditions and is extremely slow. Dutasteride does not bind to the human androgen receptor.

12.2 Pharmacodynamics

Effect on 5 Alpha-Dihydrotestosterone and Testosterone

The maximum effect of daily doses of dutasteride on the reduction of DHT is dose dependent and is observed within 1 to 2 weeks. After 1 and 2 weeks of daily dosing with dutasteride 0.5 mg, median serum DHT concentrations were reduced by 85% and 90%, respectively. In patients with BPH treated with dutasteride 0.5 mg/day for 4 years, the median decrease in serum DHT was 94% at 1 year, 93% at 2 years, and 95% at both 3 and 4 years. The median increase in serum testosterone was 19% at both 1 and 2 years, 26% at 3 years, and 22% at 4 years, but the mean and median levels remained within the physiologic range.

In patients with BPH treated with 5 mg/day of dutasteride or placebo for up to 12 weeks prior to transurethral resection of the prostate, mean DHT concentrations in prostatic tissue were significantly lower in the dutasteride group compared with placebo (784 and 5,793 pg/g, respectively, P <0.001). Mean prostatic tissue concentrations of testosterone were significantly higher in the dutasteride group compared with placebo (2,073 and 93 pg/g, respectively, P <0.001).

Adult males with genetically inherited type 2 5 alpha-reductase deficiency also have decreased DHT levels. These 5 alpha-reductase-deficient males have a small prostate gland throughout life and do not develop BPH. Except for the associated urogenital defects present at birth, no other clinical abnormalities related to 5 alpha-reductase deficiency have been observed in these individuals.

Effects on Other Hormones

In healthy volunteers, 52 weeks of treatment with dutasteride 0.5 mg/day (n = 26) resulted in no clinically significant change compared with placebo (n = 23) in sex hormone-binding globulin, estradiol, luteinizing hormone, follicle-stimulating hormone, thyroxine (free T4), and dehydroepiandrosterone. Statistically significant, baseline-adjusted mean increases compared with placebo were observed for total testosterone at 8 weeks (97.1 ng/dL, P <0.003) and thyroid-stimulating hormone at 52 weeks (0.4 mcIU/mL, P <0.05). The median percentage changes from baseline within the dutasteride group were 17.9% for testosterone at 8 weeks and 12.4% for thyroid-stimulating hormone at 52 weeks. After stopping dutasteride for 24 weeks, the mean levels of testosterone and thyroid-stimulating hormone had returned to baseline in the group of subjects with available data at the visit. In subjects with BPH treated with dutasteride in a large randomized, double-blind, placebo-controlled trial, there was a median percent increase in luteinizing hormone of 12% at 6 months and 19% at both 12 and 24 months.

Other Effects

Plasma lipid panel and bone mineral density were evaluated following 52 weeks of dutasteride 0.5 mg once daily in healthy volunteers. There was no change in bone mineral density as measured by dual energy x-ray absorptiometry compared with either placebo or baseline. In addition, the plasma lipid profile (i.e., total cholesterol, low density lipoproteins, high density lipoproteins, triglycerides) was unaffected by dutasteride. No clinically significant changes in adrenal hormone responses to adrenocorticotropic hormone (ACTH) stimulation were observed in a subset population (n = 13) of the 1-year healthy volunteer trial.

12.3 Pharmacokinetics

Absorption

Following administration of a single 0.5-mg dose of a soft gelatin capsule, time to peak serum concentrations (Tmax) of dutasteride occurs within 2 to 3 hours. Absolute bioavailability in 5 healthy subjects is approximately 60% (range: 40% to 94%). When the drug is administered with food, the maximum serum concentrations were reduced by 10% to 15%. This reduction is of no clinical significance.

Distribution

Pharmacokinetic data following single and repeat oral doses show that dutasteride has a large volume of distribution (300 to 500 L). Dutasteride is highly bound to plasma albumin (99.0%) and alpha-1 acid glycoprotein (96.6%).

In a trial of healthy subjects (n = 26) receiving dutasteride 0.5 mg/day for 12 months, semen dutasteride concentrations averaged 3.4 ng/mL (range: 0.4 to 14 ng/mL) at 12 months and, similar to serum, achieved steady-state concentrations at 6 months. On average, at 12 months 11.5% of serum dutasteride concentrations partitioned into semen.

Metabolism and Elimination

Dutasteride is extensively metabolized in humans. In vitro studies showed that dutasteride is metabolized by the CYP3A4 and CYP3A5 isoenzymes. Both of these isoenzymes produced the 4′-hydroxydutasteride, 6-hydroxydutasteride, and the 6,4′-dihydroxydutasteride metabolites. In addition, the 15-hydroxydutasteride metabolite was formed by CYP3A4. Dutasteride is not metabolized in vitro by human cytochrome P450 isoenzymes CYP1A2, CYP2A6, CYP2B6, CYP2C8, CYP2C9, CYP2C19, CYP2D6, and CYP2E1. In human serum following dosing to steady state, unchanged dutasteride, 3 major metabolites (4′-hydroxydutasteride, 1,2-dihydrodutasteride, and 6-hydroxydutasteride), and 2 minor metabolites (6,4′-dihydroxydutasteride and 15-hydroxydutasteride), as assessed by mass spectrometric response, have been detected. The absolute stereochemistry of the hydroxyl additions in the 6 and 15 positions is not known. In vitro, the 4′-hydroxydutasteride and 1,2-dihydrodutasteride metabolites are much less potent than dutasteride against both isoforms of human 5 alpha-reductase. The activity of 6β-hydroxydutasteride is comparable to that of dutasteride.

Dutasteride and its metabolites were excreted mainly in feces. As a percent of dose, there was approximately 5% unchanged dutasteride (~1% to ~15%) and 40% as dutasteride-related metabolites (~2% to ~90%). Only trace amounts of unchanged dutasteride were found in urine (<1%). Therefore, on average, the dose unaccounted for approximated 55% (range: 5% to 97%).

The terminal elimination half-life of dutasteride is approximately 5 weeks at steady state. The average steady-state serum dutasteride concentration was 40 ng/mL following 0.5 mg/day for 1 year. Following daily dosing, dutasteride serum concentrations achieve 65% of steady-state concentration after 1 month and approximately 90% after 3 months. Due to the long half-life of dutasteride, serum concentrations remain detectable (greater than 0.1 ng/mL) for up to 4 to 6 months after discontinuation of treatment.

Specific Populations

Pediatric Patients: Dutasteride pharmacokinetics have not been investigated in subjects younger than 18 years.

Geriatric Patients: No dose adjustment is necessary in the elderly. The pharmacokinetics and pharmacodynamics of dutasteride were evaluated in 36 healthy male subjects aged between 24 and 87 years following administration of a single 5‑mg dose of dutasteride. In this single‑dose trial, dutasteride half‑life increased with age (approximately 170 hours in men aged 20 to 49 years, approximately 260 hours in men aged 50 to 69 years, and approximately 300 hours in men older than 70 years). Of 2,167 men treated with dutasteride in the 3 pivotal trials, 60% were age 65 and over and 15% were age 75 and over. No overall differences in safety or efficacy were observed between these patients and younger patients.

Male and Female Patients: AVODART is contraindicated in pregnancy and is not indicated for use in women [see Contraindications (4), Warnings and Precautions (5.1)]. The pharmacokinetics of dutasteride in women have not been studied.

Racial and Ethnic Groups: The effect of race on dutasteride pharmacokinetics has not been studied.

Patients with Renal Impairment: The effect of renal impairment on dutasteride pharmacokinetics has not been studied. However, less than 0.1% of a steady‑state 0.5‑mg dose of dutasteride is recovered in human urine, so no adjustment in dosage is anticipated for patients with renal impairment.

Patients with Hepatic Impairment: The effect of hepatic impairment on dutasteride pharmacokinetics has not been studied. Because dutasteride is extensively metabolized, exposure could be higher in hepatically impaired patients.

Drug Interaction Studies

Cytochrome P450 Inhibitors: No clinical drug interaction trials have been performed to evaluate the impact of CYP3A enzyme inhibitors on dutasteride pharmacokinetics. However, based on in vitro data, blood concentrations of dutasteride may increase in the presence of inhibitors of CYP3A4/5 such as ritonavir, ketoconazole, verapamil, diltiazem, cimetidine, troleandomycin, and ciprofloxacin.

Dutasteride does not inhibit the in vitro metabolism of model substrates for the major human cytochrome P450 isoenzymes (CYP1A2, CYP2C9, CYP2C19, CYP2D6, and CYP3A4) at a concentration of 1,000 ng/mL, 25 times greater than steady-state serum concentrations in humans.

Alpha-adrenergic Antagonists: In a single-sequence, crossover trial in healthy volunteers, the administration of tamsulosin or terazosin in combination with AVODART had no effect on the steady-state pharmacokinetics of either alpha-adrenergic antagonist. Although the effect of administration of tamsulosin or terazosin on dutasteride pharmacokinetic parameters was not evaluated, the percent change in DHT concentrations was similar for AVODART alone compared with the combination treatment.

Calcium Channel Antagonists: In a population pharmacokinetics analysis, a decrease in clearance of dutasteride was noted when coadministered with the CYP3A4 inhibitors verapamil (-37%, n = 6) and diltiazem (-44%, n = 5). In contrast, no decrease in clearance was seen when amlodipine, another calcium channel antagonist that is not a CYP3A4 inhibitor, was coadministered with dutasteride (+7%, n = 4).

The decrease in clearance and subsequent increase in exposure to dutasteride in the presence of verapamil and diltiazem is not considered to be clinically significant. No dose adjustment is recommended.

Cholestyramine: Administration of a single 5-mg dose of AVODART followed 1 hour later by 12 g cholestyramine did not affect the relative bioavailability of dutasteride in 12 normal volunteers.

Digoxin: In a trial of 20 healthy volunteers, AVODART did not alter the steady-state pharmacokinetics of digoxin when administered concomitantly at a dose of 0.5 mg/day for 3 weeks.

Warfarin: In a trial of 23 healthy volunteers, 3 weeks of treatment with AVODART 0.5 mg/day did not alter the steady-state pharmacokinetics of the S- or R-warfarin isomers or alter the effect of warfarin on prothrombin time when administered with warfarin.

Other Concomitant Therapy: Although specific interaction trials were not performed with other compounds, approximately 90% of the subjects in the 3 randomized, double-blind, placebo-controlled safety and efficacy trials receiving AVODART were taking other medications concomitantly. No clinically significant adverse interactions could be attributed to the combination of AVODART and concurrent therapy when AVODART was coadministered with anti-hyperlipidemics, angiotensin-converting enzyme (ACE) inhibitors, beta-adrenergic blocking agents, calcium channel blockers, corticosteroids, diuretics, nonsteroidal anti-inflammatory drugs (NSAIDs), phosphodiesterase Type V inhibitors, and quinolone antibiotics.

13 NONCLINICAL TOXICOLOGY

13.1 Carcinogenesis, Mutagenesis, Impairment of Fertility

Carcinogenesis

A 2-year carcinogenicity study was conducted in B6C3F1 mice at doses of 3, 35, 250, and 500 mg/kg/day for males and 3, 35, and 250 mg/kg/day for females; an increased incidence of benign hepatocellular adenomas was noted at 250 mg/kg/day (290-fold the MRHD of a 0.5-mg daily dose) in female mice only. Two of the 3 major human metabolites have been detected in mice. The exposure to these metabolites in mice is either lower than in humans or is not known.

In a 2-year carcinogenicity study in Han Wistar rats, at doses of 1.5, 7.5, and 53 mg/kg/day in males and 0.8, 6.3, and 15 mg/kg/day in females, there was an increase in Leydig cell adenomas in the testes at 135-fold the MRHD (53 mg/kg/day and greater). An increased incidence of Leydig cell hyperplasia was present at 52-fold the MRHD (male rat doses of 7.5 mg/kg/day and greater). A positive correlation between proliferative changes in the Leydig cells and an increase in circulating luteinizing hormone levels has been demonstrated with 5 alpha-reductase inhibitors and is consistent with an effect on the hypothalamic-pituitary-testicular axis following 5 alpha-reductase inhibition. At tumorigenic doses, luteinizing hormone levels in rats were increased by 167%. In this study, the major human metabolites were tested for carcinogenicity at approximately 1 to 3 times the expected clinical exposure.

Mutagenesis

Dutasteride was tested for genotoxicity in a bacterial mutagenesis assay (Ames test), a chromosomal aberration assay in Chinese hamster ovary cells, and a micronucleus assay in rats. The results did not indicate any genotoxic potential of the parent drug. Two major human metabolites were also negative in either the Ames test or an abbreviated Ames test.

Impairment of Fertility

Treatment of sexually mature male rats with dutasteride at 0.1 times the MRHD (animal doses of 0.05 mg/kg/day or greater for up to 31 weeks) based on mean serum concentration resulted in dose- and time‑dependent decreases in fertility at all doses; reduced cauda epididymal (absolute) sperm counts but not sperm concentration (at 50 and 500 mg/kg/day); reduced weights of the epididymis, prostate, and seminal vesicles; and microscopic changes (cytoplasmic vacuolation of tubular epithelium in the epididymides and/or decreased cytoplasmic content of epithelium, consistent with decreased secretory activity in the prostate and seminal vesicles) in the reproductive organs at all doses in the absence of paternal toxicity. The fertility effects were reversed by Recovery Week 6 at all doses, and sperm counts were normal at the end of a 14‑week recovery period. The microscopic changes were no longer present at Recovery Week 14 at 0.1 times the MRHD and were partly recovered in the remaining treatment groups. Low levels of dutasteride (0.6 to 17 ng/mL) were detected in the serum of untreated female rats mated to treated males (10 to 500 mg/kg/day for 29 to 30 weeks) which are 16 to 110 times the MRHD based on mean serum concentration. No feminization occurred in male offspring of untreated female rats mated to treated male rats even though detectable blood levels of dutasteride were observed in the female rats.

In a fertility study in female rats with dosing 4 weeks prior to mating through early gestation, oral administration of dutasteride at doses of 0.05, 2.5, 12.5, and 30 mg/kg/day resulted in reduced litter size due to increased resorptions and in feminization of male fetuses (decreased anogenital distance) at 2- to 10 times the MRHD (animal doses of 2.5 mg/kg/day or greater) based on mean serum concentration, in the presence of maternal toxicity (decreased body weight gain). Fetal body weights were also reduced at approximately 0.02 times the MRHD (rat dose of 0.05 mg/kg/day or greater) based on mean serum concentration, with no no-effect level, in the absence of maternal toxicity.

13.2 Animal Toxicology and/or Pharmacology

Central Nervous System Toxicology Studies

In rats and dogs, repeated oral administration of dutasteride resulted in some animals showing signs of non-specific, reversible, centrally-mediated toxicity without associated histopathological changes at exposures 425- and 315-fold the expected clinical exposure (of parent drug), respectively.

Rabbit Dermal Absorption

In a rabbit dermal pharmacokinetics study, dermal absorption of dutasteride in CAPMUL (glyceryl oleate) in rabbits resulted in serum concentrations of 2.7 to 40.5 mcg/h/mL for doses of 1 to 20 mg/mL, respectively, or 56% to 100% of applied dutasteride to be absorbed under occluded and prolonged conditions. AVODART soft gelatin capsules administered orally contain 0.5 mg dutasteride dissolved in a mixture of mono‑di‑glycerides of caprylic/capric acid and butylated hydroxytoluene. Dutasteride in water was minimally absorbed in rabbits (2,000 mg/kg).

14 CLINICAL STUDIES

14.1 Monotherapy

AVODART 0.5 mg/day (n = 2,167) or placebo (n = 2,158) was evaluated in male subjects with BPH in three 2‑year multicenter, placebo‑controlled, double‑blind trials, each with 2‑year open‑label extensions (n = 2,340). More than 90% of the trial population was white. Subjects were aged at least 50 years with a serum PSA ≥1.5 ng/mL and <10 ng/mL and BPH diagnosed by medical history and physical examination, including enlarged prostate (≥30 cc) and BPH symptoms that were moderate to severe according to the American Urological Association Symptom Index (AUA‑SI). Most of the 4,325 subjects randomly assigned to receive either dutasteride or placebo completed 2 years of double‑blind treatment (70% and 67%, respectively). Most of the 2,340 subjects in the trial extensions completed 2 additional years of open‑label treatment (71%).

Effect on Symptom Scores

Symptoms were quantified using the AUA-SI, a questionnaire that evaluates urinary symptoms (incomplete emptying, frequency, intermittency, urgency, weak stream, straining, and nocturia) by rating on a 0 to 5 scale for a total possible score of 35, with higher numerical total symptom scores representing greater severity of symptoms. The baseline AUA-SI score across the 3 trials was approximately 17 units in both treatment groups.

Subjects receiving dutasteride achieved statistically significant improvement in symptoms versus placebo by Month 3 in 1 trial and by Month 12 in the other 2 pivotal trials. At Month 12, the mean decrease from baseline in AUA‑SI total symptom scores across the 3 trials pooled was ‑3.3 units for dutasteride and ‑2.0 units for placebo with a mean difference between the 2 treatment groups of ‑1.3 (range: ‑1.1 to ‑1.5 units in each of the 3 trials, P <0.001) and was consistent across the 3 trials. At Month 24, the mean decrease from baseline was ‑3.8 units for dutasteride and ‑1.7 units for placebo with a mean difference of -2.1 (range: ‑1.9 to ‑2.2 units in each of the 3 trials, P <0.001). See Figure 1. The improvement in BPH symptoms seen during the first 2 years of double‑blind treatment was maintained throughout an additional 2 years of open‑label extension trials.

These trials were prospectively designed to evaluate effects on symptoms based on prostate size at baseline. In men with prostate volumes ≥40 cc, the mean decrease was -3.8 units for dutasteride and -1.6 units for placebo, with a mean difference between the 2 treatment groups of -2.2 at Month 24. In men with prostate volumes <40 cc, the mean decrease was -3.7 units for dutasteride and -2.2 units for placebo, with a mean difference between the 2 treatment groups of -1.5 at Month 24.

Figure 1. AUA-SI Scorea Change from Baseline (Randomized, Double-blind, Placebo-Controlled Trials Pooled)

a AUA-SI score ranges from 0 to 35.

Effect on Acute Urinary Retention and the Need for BPH-Related Surgery

Efficacy was also assessed after 2 years of treatment by the incidence of AUR requiring catheterization and BPH‑related urological surgical intervention. Compared with placebo, AVODART was associated with a statistically significantly lower incidence of AUR (1.8% for AVODART versus 4.2% for placebo, P <0.001; 57% reduction in risk, [95% CI: 38% to 71%]) and with a statistically significantly lower incidence of surgery (2.2% for AVODART versus 4.1% for placebo, P <0.001; 48% reduction in risk, [95% CI: 26% to 63%]). See Figures 2 and 3.

Figure 2. Percent of Subjects Developing Acute Urinary Retention over a 24-Month Period (Randomized, Double-blind, Placebo-Controlled Trials Pooled)

Figure 3. Percent of Subjects Having Surgery for Benign Prostatic Hyperplasia over a 24-Month Period (Randomized, Double-blind, Placebo-Controlled Trials Pooled)

Effect on Prostate Volume

A prostate volume of at least 30 cc measured by transrectal ultrasound was required for trial entry. The mean prostate volume at trial entry was approximately 54 cc.

Statistically significant differences (AVODART versus placebo) were noted at the earliest post-treatment prostate volume measurement in each trial (Month 1, Month 3, or Month 6) and continued through Month 24. At Month 12, the mean percent change in prostate volume across the 3 trials pooled was -24.7% for dutasteride and -3.4% for placebo; the mean difference (dutasteride minus placebo) was -21.3% (range: -21.0% to -21.6% in each of the 3 trials, P <0.001). At Month 24, the mean percent change in prostate volume across the 3 trials pooled was -26.7% for dutasteride and -2.2% for placebo with a mean difference of -24.5% (range: ‑24.0% to ‑25.1% in each of the 3 trials, P <0.001). See Figure 4. The reduction in prostate volume seen during the first 2 years of double-blind treatment was maintained throughout an additional 2 years of open‑label extension trials.

Figure 4. Prostate Volume Percent Change from Baseline (Randomized, Double-blind, Placebo-Controlled Trials Pooled)

Effect on Maximum Urine Flow Rate

A mean peak urine flow rate (Qmax) of ≤15 mL/sec was required for trial entry. Qmax was approximately 10 mL/sec at baseline across the 3 pivotal trials.

Differences between the 2 groups were statistically significant from baseline at Month 3 in all 3 trials and were maintained through Month 12. At Month 12, the mean increase in Qmax across the 3 trials pooled was 1.6 mL/sec for AVODART and 0.7 mL/sec for placebo; the mean difference (dutasteride minus placebo) was 0.8 mL/sec (range: 0.7 to 1.0 mL/sec in each of the 3 trials, P <0.001). At Month 24, the mean increase in Qmax was 1.8 mL/sec for dutasteride and 0.7 mL/sec for placebo, with a mean difference of 1.1 mL/sec (range: 1.0 to 1.2 mL/sec in each of the 3 trials, P <0.001). See Figure 5. The increase in maximum urine flow rate seen during the first 2 years of double‑blind treatment was maintained throughout an additional 2 years of open-label extension trials.

Figure 5. Qmax Change from Baseline (Randomized, Double-blind, Placebo-Controlled Trials Pooled)

Summary of Clinical Trials

Data from 3 large, well-controlled efficacy trials demonstrate that treatment with AVODART (0.5 mg once daily) reduces the risk of both AUR and BPH-related surgical intervention relative to placebo, improves BPH-related symptoms, decreases prostate volume, and increases maximum urinary flow rates. These data suggest that AVODART arrests the disease process of BPH in men with an enlarged prostate.

14.2 Combination with Alpha-blocker Therapy (CombAT)

The efficacy of combination therapy (AVODART 0.5 mg/day plus tamsulosin 0.4 mg/day, n = 1,610) was compared with AVODART alone (n = 1,623) or tamsulosin alone (n = 1,611) in a 4‑year multicenter, randomized, double‑blind trial. Trial entry criteria were similar to the double‑blind, placebo‑controlled monotherapy efficacy trials described in Section 14.1. Eighty‑eight percent (88%) of the enrolled trial population was white. Approximately 52% of subjects had previous exposure to 5 alpha‑reductase–inhibitor or alpha-adrenergic–antagonist treatment. Of the 4,844 subjects randomly assigned to receive treatment, 69% of subjects in the combination group, 67% in the group receiving AVODART, and 61% in the tamsulosin group completed 4 years of double‑blind treatment.

Effect on Symptom Score

Symptoms were quantified using the first 7 questions of the International Prostate Symptom Score (IPSS) (identical to the AUA‑SI). The baseline score was approximately 16.4 units for each treatment group. Combination therapy was statistically superior to each of the monotherapy treatments in decreasing symptom score at Month 24, the primary time point for this endpoint. At Month 24 the mean changes from baseline (±SD) in IPSS total symptom scores were -6.2 (±7.14) for combination, -4.9 (±6.81) for AVODART, and -4.3 (±7.01) for tamsulosin, with a mean difference between combination and AVODART of ‑1.3 units (P <0.001; [95% CI: ‑1.69, ‑0.86]), and between combination and tamsulosin of ‑1.8 units (P <0.001; [95% CI: ‑2.23, ‑1.40]). A significant difference was seen by Month 9 and continued through Month 48. At Month 48 the mean changes from baseline (±SD) in IPSS total symptom scores were -6.3 (±7.40) for combination, -5.3 (±7.14) for AVODART, and -3.8 (±7.74) for tamsulosin, with a mean difference between combination and AVODART of ‑0.96 units (P <0.001; [95% CI: ‑1.40, ‑0.52]), and between combination and tamsulosin of ‑2.5 units (P <0.001; [95% CI: ‑2.96, ‑2.07]). See Figure 6.

Figure 6. International Prostate Symptom Score Change from Baseline over a 48-Month Period (Randomized, Double-blind, Parallel-Group Trial [CombAT Trial])

Effect on Acute Urinary Retention or the Need for BPH-Related Surgery

After 4 years of treatment, combination therapy with AVODART and tamsulosin did not provide benefit over monotherapy with AVODART in reducing the incidence of AUR or BPH-related surgery.

Effect on Maximum Urine Flow Rate

The baseline Qmax was approximately 10.7 mL/sec for each treatment group. Combination therapy was statistically superior to each of the monotherapy treatments in increasing Qmax at Month 24, the primary time point for this endpoint. At Month 24, the mean increases from baseline (±SD) in Qmax were 2.4 (±5.26) mL/sec for combination, 1.9 (±5.10) mL/sec for AVODART, and 0.9 (±4.57) mL/sec for tamsulosin, with a mean difference between combination and AVODART of 0.5 mL/sec (P = 0.003; [95% CI: 0.17, 0.84]), and between combination and tamsulosin of 1.5 mL/sec (P <0.001; [95% CI: 1.19, 1.86]). This difference was seen by Month 6 and continued through Month 24. See Figure 7.

The additional improvement in Qmax of combination therapy over monotherapy with AVODART was no longer statistically significant at Month 48.

Figure 7. Qmax Change from Baseline over a 24-Month Period (Randomized, Double-blind, Parallel-Group Trial [CombAT Trial])

Effect on Prostate Volume

The mean prostate volume at trial entry was approximately 55 cc. At Month 24, the primary time point for this endpoint, the mean percent changes from baseline (±SD) in prostate volume were -26.9% (±22.57) for combination therapy, -28.0% (±24.88) for AVODART, and 0% (±31.14) for tamsulosin, with a mean difference between combination and AVODART of 1.1% (P = NS; [95% CI: -0.6, 2.8]), and between combination and tamsulosin of -26.9% (P <0.001; [95% CI: -28.9, -24.9]). Similar changes were seen at Month 48: -27.3% (±24.91) for combination therapy, -28.0% (±25.74) for AVODART, and +4.6% (±35.45) for tamsulosin.

16 HOW SUPPLIED/STORAGE AND HANDLING

AVODART soft gelatin capsules 0.5 mg are oblong, opaque, dull yellow, gelatin capsules imprinted with “GX CE2” with red edible ink on one side, packaged in bottles of 30 (NDC 80725-712-15) and 90 (NDC 80725-712-04) with child-resistant closures.

Store at 25°C (77°F); excursions permitted to 15° to 30°C (59° to 86°F) [see USP Controlled Room Temperature].

Dutasteride is absorbed through the skin. AVODART capsules should not be handled by women who are pregnant or who could become pregnant because of the potential for absorption of dutasteride and the subsequent potential risk to a developing male fetus [see Warnings and Precautions (5.4)].

17 PATIENT COUNSELING INFORMATION

Advise the patient to read the FDA-approved patient labeling (Patient Information).

PSA Monitoring

Inform patients that AVODART reduces serum PSA levels by approximately 50% within 3 to 6 months of therapy, although it may vary for each individual. For patients undergoing PSA screening, increases in PSA levels while on treatment with AVODART may signal the presence of prostate cancer and should be evaluated by a healthcare provider [see Warnings and Precautions (5.1)].

Increased Risk of High-grade Prostate Cancer

Inform patients that there was an increase in high-grade prostate cancer in men treated with 5 alpha-reductase inhibitors (which are indicated for BPH treatment), including AVODART, compared with those treated with placebo in trials looking at the use of these drugs to reduce the risk of prostate cancer [see Indications and Usage (1.3), Warnings and Precautions (5.2), Adverse Reactions (6.1)].

Transdermal Exposure of AVODART in Pregnant or Potentially Pregnant Women—Risk to Male Fetus

Inform patients that AVODART capsules should not be handled by women who are pregnant or may potentially be pregnant because of the potential for absorption of dutasteride and the subsequent potential risk to a developing male fetus. Dutasteride can be absorbed through the skin and could result in unintended fetal exposure. If a pregnant or potentially pregnant woman comes in contact with leaking AVODART capsules, the contact area should be washed immediately with soap and water [see Warnings and Precautions (5.4), Use in Specific Populations (8.1)].

Effects on Semen Parameters

Advise men that AVODART may affect sperm characteristics but the effect on fertility is unknown [see Warnings and Precautions (5.6), Use in Specific Populations (8.3)].

Blood Donation

Inform men treated with AVODART that they should not donate blood until at least 6 months following their last dose to prevent pregnant women from receiving dutasteride through blood transfusion [see Warnings and Precautions (5.5)]. Serum levels of dutasteride are detectable for 4 to 6 months after treatment ends [see Clinical Pharmacology (12.3)].

AVODART is a trademark used under license by Waylis Therapeutics LLC.

The other brands listed are trademarks owned by or licensed to their respective owners and are not owned by or licensed to Waylis Therapeutics LLC. The makers of these brands are not affiliated with and do not endorse Waylis Therapeutics LLC or its products.

Manufactured for:

Waylis Therapeutics LLC
Wixom, MI 48393

PHARMACIST-DETACH HERE AND GIVE INSTRUCTIONS TO PATIENT

----------------------------------------------------------------------------------------------------------

PATIENT INFORMATION

AVODART (av’ ō dart)

(dutasteride) capsules

AVODART is for use by men only.

What is AVODART?

AVODART is a prescription medicine that contains dutasteride. AVODART is used to treat the symptoms of benign prostatic hyperplasia (BPH) in men with an enlarged prostate to:

- improve symptoms,
- reduce the risk of acute urinary retention (a complete blockage of urine flow),
- reduce the risk of the need for BPH-related surgery.

Prostate growth is caused by a hormone in the blood called dihydrotestosterone (DHT). AVODART lowers DHT production in the body, leading to shrinkage of the enlarged prostate in most men. While some men have fewer problems and symptoms after 3 months of treatment with AVODART, a treatment period of at least 6 months is usually necessary to see if AVODART will work for you.

Do not take AVODART if you are:

- pregnant or may be pregnant. AVODART may harm your unborn baby. Pregnant women should not touch AVODART capsules. If a woman who is pregnant with a male baby gets enough AVODART in her body by swallowing or touching AVODART, the male baby may be born with sex organs that are not normal. If a pregnant woman comes in contact with leaking AVODART capsules, the contact area should be washed immediately with soap and water.
- allergic to dutasteride or any of the ingredients in AVODART. See the end of this leaflet for a complete list of ingredients in AVODART.
- allergic to other 5 alpha-reductase inhibitors, for example, PROSCAR (finasteride) tablets.

Before you take AVODART, tell your healthcare provider about all of your medical conditions, including if you:

- have liver problems

Tell your healthcare provider about all the medicines you take, including prescription and over-the-counter medicines, vitamins, and herbal supplements. AVODART and other medicines may affect each other, causing side effects. AVODART may affect the way other medicines work, and other medicines may affect how AVODART works.

Know the medicines you take. Keep a list of them to show your healthcare provider and pharmacist when you get a new medicine.

How should I take AVODART?

- Take 1 AVODART capsule once a day.
- Swallow AVODART capsules whole. Do not crush, chew, or open AVODART capsules because the contents of the capsule may irritate your lips, mouth, or throat.
- You can take AVODART with or without food.
- If you miss a dose, you may take it later that day. Do not make up the missed dose by taking 2 doses the next day.

What should I avoid while taking AVODART?

- You should not donate blood while taking AVODART or for 6 months after you have stopped AVODART. This is important to prevent pregnant women from receiving AVODART through blood transfusions.

What are the possible side effects of AVODART?

AVODART may cause serious side effects, including:

- Rare and serious allergic reactions, including:
  - Swelling of your face, tongue, or throat
  - Serious skin reactions, such as skin peeling
Get medical help right away if you have these serious allergic reactions.
- Higher chance of a more serious form of prostate cancer.

The most common side effects of AVODART include:

- trouble getting or keeping an erection (impotence)*
- a decrease in sex drive (libido)*
- ejaculation problems*
- enlarged or painful breasts. If you notice breast lumps or nipple discharge, you should talk to your healthcare provider.

*Some of these events may continue after you stop taking AVODART.

Depressed mood has been reported in patients receiving AVODART.

AVODART has been shown to reduce sperm count, semen volume, and sperm movement. However, the effect of AVODART on male fertility is not known.

Prostate-Specific Antigen (PSA) Test: Your healthcare provider may check you for other prostate problems, including prostate cancer, before you start and while you take AVODART. A blood test called PSA (prostate-specific antigen) is sometimes used to see if you might have prostate cancer. AVODART will reduce the amount of PSA measured in your blood. Your healthcare provider is aware of this effect and can still use PSA to see if you might have prostate cancer. Increases in your PSA levels while on treatment with AVODART (even if the PSA levels are in the normal range) should be evaluated by your healthcare provider.

These are not all the possible side effects of AVODART. Call your doctor for medical advice about side effects. You may report side effects to FDA at 1‑800‑FDA‑1088.

How should I store AVODART?

- Store AVODART capsules at room temperature (59°F to 86°F or 15°C to 30°C).
- AVODART capsules may become deformed and/or discolored if kept at high temperatures.
- Do not use AVODART if your capsules are deformed, discolored, or leaking.
- Safely throw away medicine that is no longer needed.

Keep AVODART and all medicines out of the reach of children.

General information about the safe and effective use of AVODART.

Medicines are sometimes prescribed for purposes other than those listed in a Patient Information leaflet. Do not use AVODART for a condition for which it was not prescribed. Do not give AVODART to other people, even if they have the same symptoms that you have. It may harm them.

You can ask your healthcare provider or pharmacist for information about AVODART that is written for health professionals.

For more information call 1-888-825-5249.

What are the ingredients in AVODART?

Active ingredient: dutasteride

Inactive ingredients: butylated hydroxytoluene, ferric oxide (yellow), gelatin (from certified BSE‑free bovine sources), glycerin, mono‑di‑glycerides of caprylic/capric acid, titanium dioxide, and edible red ink.

Manufactured for:
Waylis Therapeutics LLC
Wixom, MI 48393

AVODART is a trademark under license by Waylis Therapeutics LLC. The other brand listed is a trademark owned by or licensed to its respective owner and is not a trademark owned by or licensed to Waylis Therapeutics LLC. The maker of this brand is not affiliated with and does not endorse Waylis Therapeutics LLC or its products.

This Patient Information has been approved by the U.S. Food and Drug Administration.

Revised: 10/2023

PACKAGE LABEL

PRINCIPAL DISPLAY PANEL

NDC 80725-712-04

AVODART®

(dutasteride)

Soft Gelatin Capsules

0.5 mg

RX only

GX CE2

90 Capsules

WARNING: AVODART should not be used by women or children. Women who are or may potentially be pregnant should not use or handle AVODART Soft Gelatin Capsules (see prescribing information). If contact is made with leaking capsule, wash immediately with soap and water.

Each capsule contains 0.5 mg dutasteride.

Usual Dosage: 0.5 mg once a day.

Capsules should be swallowed whole and not chewed or opened. See prescribing information for further dosing information.

Store at 25oC (77oF); excursions permitted to 15-30oC (59-86oF) [see USP Controlled Room Temperature].

Dispense in a well-closed container as defined in the USP.

Do not use if printed safety seal under cap is broken or missing.

Manufactured for:
Waylis Therapeutics LLC
Wixom, MI 48393

Rev. 10/23